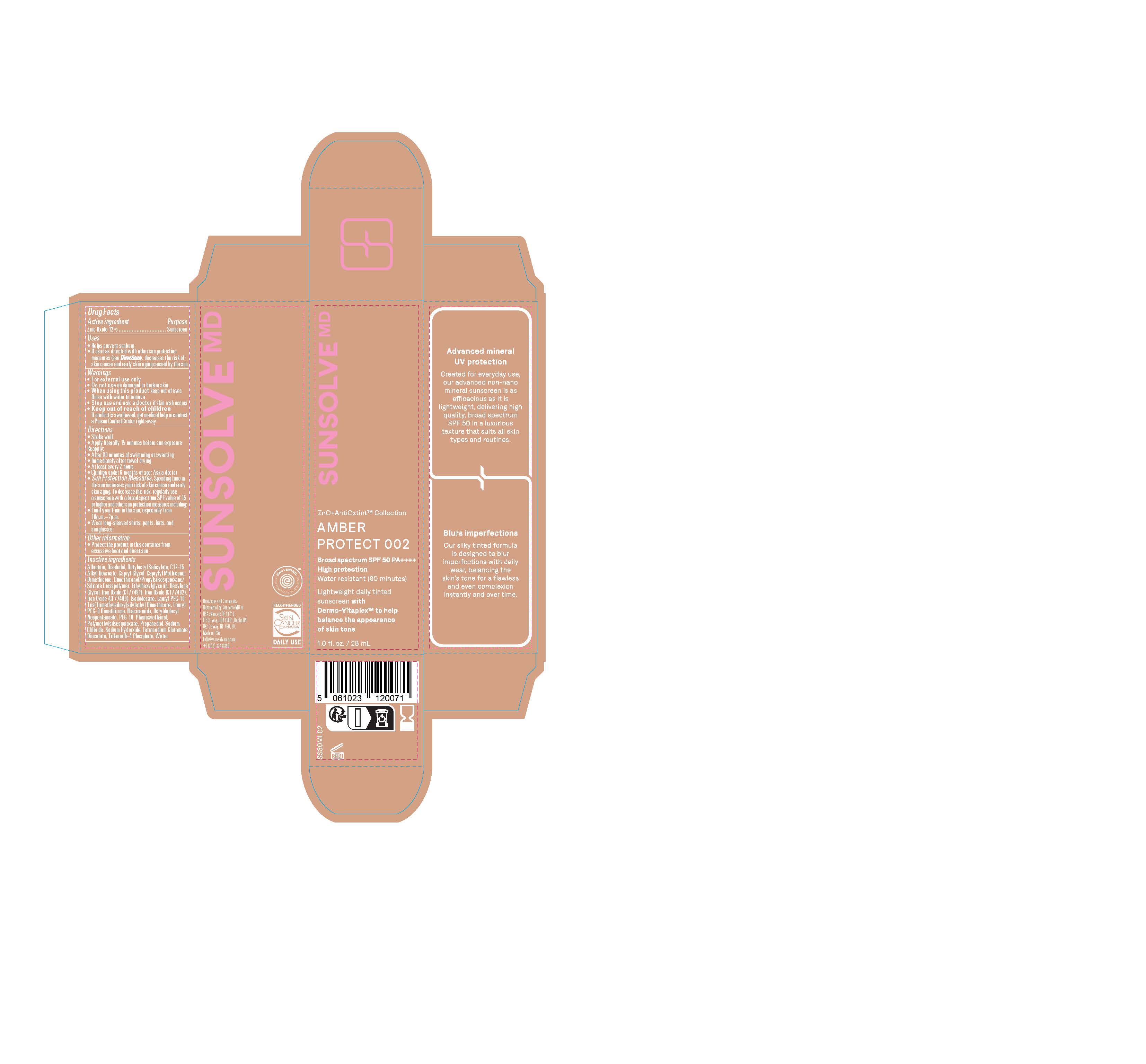 DRUG LABEL: Sunsolve MD Mineral Shade Amber 002
NDC: 84878-402 | Form: LOTION
Manufacturer: Sunsolve MD Inc
Category: otc | Type: HUMAN OTC DRUG LABEL
Date: 20251114

ACTIVE INGREDIENTS: ZINC OXIDE 132 mg/1 mL
INACTIVE INGREDIENTS: TRILAURETH-4 PHOSPHATE; BUTYLOCTYL SALICYLATE; OCTYLDODECYL NEOPENTANOATE; ISODODECANE; .ALPHA.-BISABOLOL, (+)-; SODIUM HYDROXIDE; WATER; NIACINAMIDE; ETHYLHEXYLGLYCERIN; HEXYLENE GLYCOL; GLYCERIN; DIMETHICONOL/PROPYLSILSESQUIOXANE/SILICATE CROSSPOLYMER (450000000 MW); PROPANEDIOL; TETRASODIUM GLUTAMATE DIACETATE; SODIUM CHLORIDE; PHENOXYETHANOL; POLYMETHYLSILSESQUIOXANE (4.5 MICRONS); ALKYL (C12-15) BENZOATE; FERRIC OXIDE YELLOW; ALLANTOIN; PEG-10; CAPRYLYL METHICONE; DIMETHICONE; LAURYL PEG-8 DIMETHICONE (300 CPS); FERRIC OXIDE RED; FERROSOFERRIC OXIDE; CAPRYLYL GLYCOL

Sunsolve MD Mineral Shade Amber 002